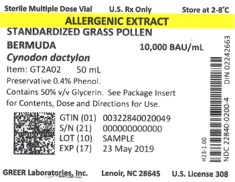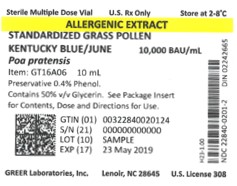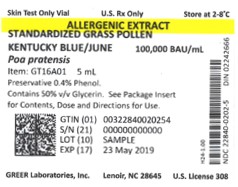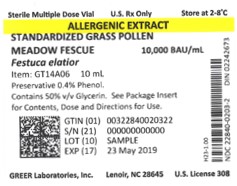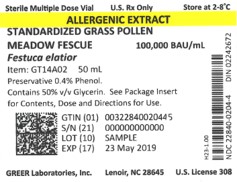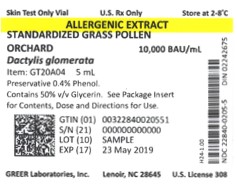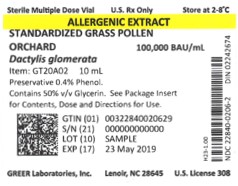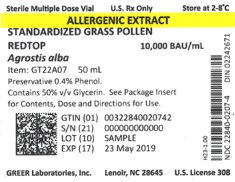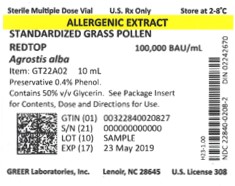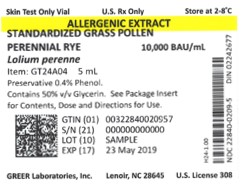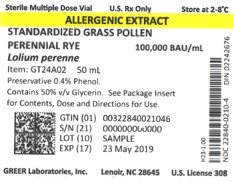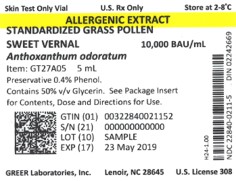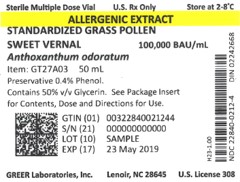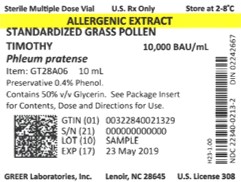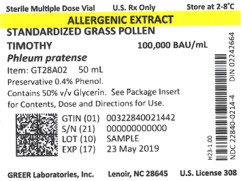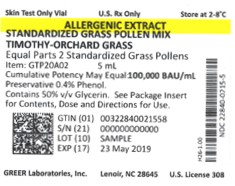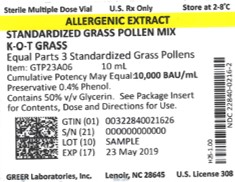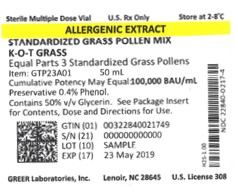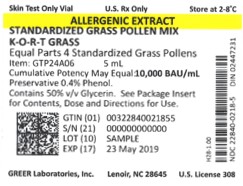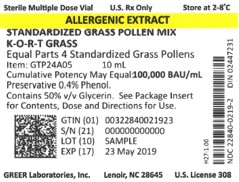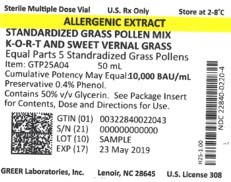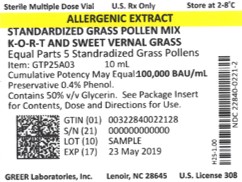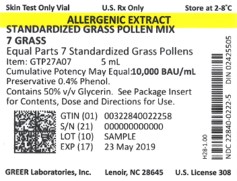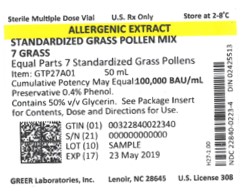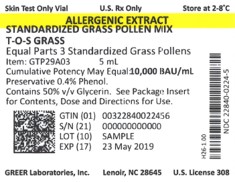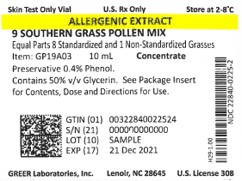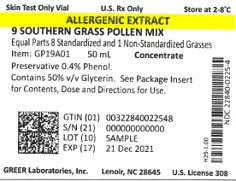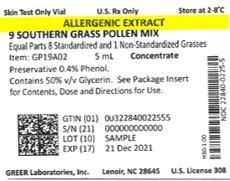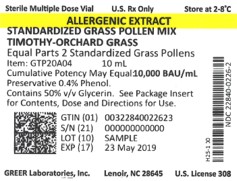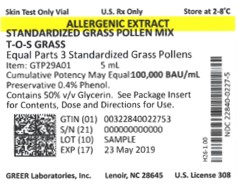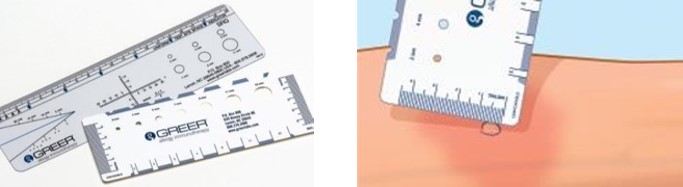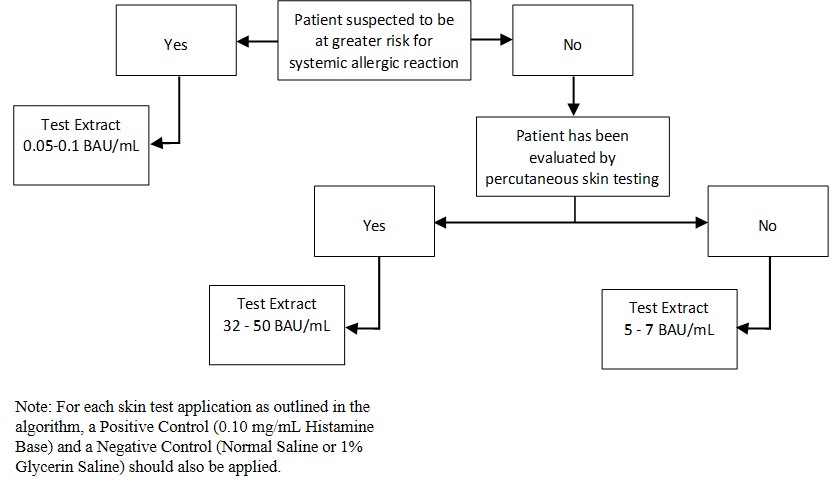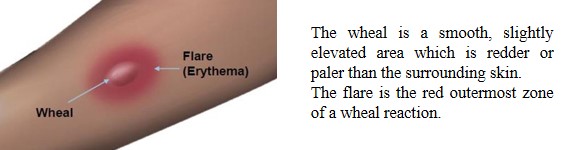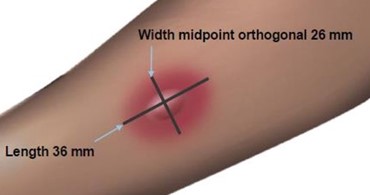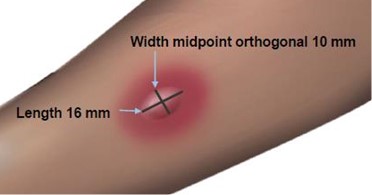 DRUG LABEL: Timothy-Orchard Standardized Grass Pollen Mix
NDC: 22840-0215 | Form: SOLUTION
Manufacturer: Greer Laboratories, Inc.
Category: other | Type: STANDARDIZED ALLERGENIC
Date: 20250610

ACTIVE INGREDIENTS: DACTYLIS GLOMERATA POLLEN 50000 [BAU]/1 mL; PHLEUM PRATENSE POLLEN 50000 [BAU]/1 mL
INACTIVE INGREDIENTS: SODIUM CHLORIDE; SODIUM BICARBONATE; PHENOL; GLYCERIN

Standardized Grass Pollen Allergenic Extracts

HIGHLIGHTS OF PRESCRIBING INFORMATION

These highlights do not include all the information needed to use Standardized Grass Pollen Allergenic Extracts safely and effectively. See full prescribing information for Standardized Grass Pollen Allergenic Extracts.

Standardized Bermuda Grass Pollen (Cynodon dactylon)

Standardized Kentucky Blue (June) Grass Pollen (Poa pratensis)

Standardized Meadow Fescue Grass Pollen (Festuca elatior)

Standardized Orchard Grass Pollen (Dactylis glomerata)

Standardized Perennial Rye Grass Pollen (Lolium perenne)

Standardized Redtop Grass Pollen (Agrostis alba)

Standardized Sweet Vernal Grass Pollen (Anthoxanthum odoratum)

Standardized Timothy Grass Pollen (Phleum pratense)

Solutions for percutaneous, intradermal or subcutaneous administration.

Initial U.S. Approval: 1997

WARNING: SEVERE ALLERGIC REACTIONS

See full prescribing information for complete boxed warning.

- Standardized Grass Pollen Allergenic Extracts can cause severe life-threatening systemic reactions, including anaphylaxis. (5.1)
- Do not administer Standardized Grass Pollen Allergenic Extracts to patients with severe, unstable or uncontrolled asthma. (4)
- Observe patients in the office for at least 30 minutes following treatment. Emergency measures and personnel trained in their use must be available immediately in the event of a life-threatening reaction. (5.1)
- Patients with extreme sensitivity to these products, on an accelerated immunotherapy build-up, switching to another lot, receiving high doses of Standardized Grass Pollen Allergenic Extracts, and patients exposed to similar allergens may be at increased risk of a severe allergic reaction. (5.1)
- Standardized Grass Pollen Allergenic Extracts may not be suitable for patients with certain underlying medical conditions that may reduce their ability to survive a systemic allergic reaction, and for patients receiving medications such as beta-blockers that may make them unresponsive to epinephrine or inhaled bronchodilators. (5.1, 5.2)

INDICATIONS AND USAGE

Standardized Grass Pollen Allergenic Extracts are indicated for:

Skin test diagnosis of patients with a clinical history of allergy to one or more of the following grass pollens: Bermuda, Kentucky Blue (June), Meadow Fescue, Orchard, Perennial Rye, Redtop, Sweet Vernal, Timothy. (1)

Immunotherapy for the reduction of grass pollen-induced allergic symptoms confirmed by positive skin test or by in vitro testing for pollen-specific IgE antibodies for Bermuda grass pollen, Kentucky Blue (June) grass pollen, Meadow Fescue grass pollen, Orchard grass pollen, Perennial Rye grass pollen, Redtop grass pollen, Sweet Vernal grass pollen, or Timothy grass pollen. (1)

DOSAGE AND ADMINISTRATION

For percutaneous, intradermal or subcutaneous use only.

The extracts are diluted with sterile diluents when used for intradermal testing or subcutaneous immunotherapy. For percutaneous testing, the extracts are diluted with sterile diluents in patients expected to be at greater risk for systemic allergic reaction. Dosages vary by mode of administration and by individual response. See full prescribing information for instructions on preparation, administration, and adjustments of dose. (2.1)

DOSAGE FORMS AND STRENGTHS

Standardized Bermuda Grass Pollen Allergenic Extract solution is available only at 10,000 Bioequivalent Allergy Units (BAU)/milliliter. (3)

Other Standardized Grass Pollen Allergenic Extract solutions are available as stock concentrates at 10,000 and 100,000 BAU/milliliter. (3)

CONTRAINDICATIONS

- Severe, unstable or uncontrolled asthma. (4)
- History of any severe systemic allergic reaction or any severe local reaction to subcutaneous allergen immunotherapy. (4)

WARNINGS AND PRECAUTIONS

Severe allergic reactions have occurred following the administration of other allergenic extracts and may occur in individuals following the administration of Standardized Grass Pollen Allergenic Extracts in the following situations:

- Extreme sensitivity to Standardized Grass Pollen Allergenic Extracts, receipt of high doses of Standardized Grass Pollen Allergenic Extracts, or concomitant exposure to similar environmental allergens. (5.1)
- Receiving an accelerated immunotherapy build-up schedule (e.g., “rush” immunotherapy) or changing from one allergenic lot to another. (5.1)

ADVERSE REACTIONS

The most common adverse reactions, occurring in over 26 to 82% of all patients who receive subcutaneous immunotherapy, are local adverse reactions at the injection site (e.g., erythema, itching, swelling, tenderness, pain). (6)

Systemic adverse reactions, occurring in ≤ 7% of patients, include generalized skin erythema, urticaria, pruritus, angioedema, rhinitis, wheezing, laryngeal edema, and hypotension. These can be fatal. (6)

To report SUSPECTED ADVERSE REACTIONS, contact GREER Laboratories, Inc. at 1-855-274-1322 or FDA at 1-800-FDA-1088 or www.fda.gov/medwatch.

DRUG INTERACTIONS

- Antihistamines and other medications that suppress histamine, including topical corticosteroids, topical anesthetics and tricyclic antidepressants can interfere with skin test results. (7)

See 17 for PATIENT COUNSELING INFORMATION

FULL PRESCRIBING INFORMATION

WARNING: SEVERE ALLERGIC REACTIONS

- Standardized Grass Pollen Allergenic Extracts can cause severe life-threatening systemic reactions, including anaphylaxis. (5.1)
- Do not administer Standardized Grass Pollen Allergenic Extracts to patients with severe, unstable, or uncontrolled asthma. (4)
- Observe patients in the office for at least 30 minutes following treatment.Emergency measures and personnel trained in their use must be available immediately in the event of a life-threatening reaction. (5.1)
- Patients with extreme sensitivity, to Standardized Grass Pollen Allergenic Extracts, those on an accelerated immunotherapy build-up schedule, those switching to another allergenic lot, those receiving high doses of the Standardized Grass Pollen Allergenic Extracts, or those also exposed to similar allergens may be at increased risk of a severe allergic reaction. (5.1)
- Standardized Grass Pollen Allergenic Extracts may not be suitable for patients with certain underlying medical conditions that may reduce their ability to survive a serious allergic reaction. (5.1)
- Standardized Grass Pollen Allergenic Extracts may not be suitable for patients who may be unresponsive to epinephrine or inhaled bronchodilators, such as those taking beta‑blockers. (5.2)

1 INDICATIONS AND USAGE

GREER Standardized Grass Pollen Allergenic Extracts are indicated for:

- Skin test diagnosis of patients with a clinical history of allergy to one or more of the following grass pollens: Bermuda, Kentucky Blue (June), Meadow Fescue, Orchard, Perennial Rye, Redtop, Sweet Vernal, Timothy.
- Immunotherapy for the reduction of grass pollen-induced allergic symptoms confirmed by positive skin test or by in vitro testing for pollen-specific IgE antibodies for Bermuda grass pollen, Kentucky Blue (June) grass pollen, Meadow Fescue grass pollen, Orchard grass pollen, Perennial Rye grass pollen, Redtop grass pollen, Sweet Vernal grass pollen, or Timothy grass pollen.

2 DOSAGE AND ADMINISTRATION

For percutaneous, intradermal or subcutaneous use only.

The extracts are diluted with sterile diluents when used for intradermal testing or subcutaneous immunotherapy. For percutaneous testing, the extracts are diluted with sterile diluents in patients expected to be at greater risk for systemic allergic reaction. Dosages vary by mode of administration and by individual response.

2.1 Preparation for Administration

Parenteral drug products should be inspected visually for particulate matter and discoloration prior to administration, whenever solution and container permit. Discard solution if either of these conditions exist.

The extracts are diluted with sterile diluents when used for percutaneous and intradermal testing, or for subcutaneous immunotherapy.

Undiluted 10,000 BAU/milliliter or 100,000 BAU/milliliter stock concentrates are used for percutaneous testing. To prepare 10-fold dilutions for percutaneous testing in patients suspected to be at greater risk for systemic allergic reaction, start with a 10,000 BAU/milliliter or 100,000 BAU/milliliter stock concentrate. Proceed as shown in Table 1. The 10-fold dilution series uses 0.5 milliliters of concentrate added to 4.5 milliliters of sterile 50% glycerin diluent. Subsequent dilutions are made in a similar manner.

To prepare 10-fold dilutions for intradermal testing and immunotherapy, start with a 10,000 BAU/milliliter or 100,000 BAU/milliliter stock concentrate. Proceed as shown in Table 1. The 10-fold dilution series uses 0.5 milliliters of concentrate added to 4.5 milliliters of sterile diluent (glycerin-free diluents for intradermal testing, glycerin-free or 10% glycerin-saline diluents for immunotherapy). Subsequent dilutions are made in a similar manner.

Table 1: 10-fold Dilution Series*
Dilution | Extract | Milliliters of Diluent | Dilution Strength (BAU/mL) | Dilution Strength (BAU/mL
0 | Concentrate |  | 100,000 | 10,000
1 | 0.5 mL Concentrate | 4.5 | 10,000 | 1,000
2 | 0.5 mL Dilution 1 | 4.5 | 1,000 | 100
3 | 0.5 mL Dilution 2 | 4.5 | 100 | 10
4 | 0.5 mL Dilution 3 | 4.5 | 10 | 1
5 | 0.5 mL Dilution 4 | 4.5 | 1 | 0.1
6 | 0.5 mL Dilution 5 | 4.5 | 0.1 | 0.01

Undiluted 10,000 BAU/milliliter or 100,000 BAU/milliliter stock concentrates are used for percutaneous testing. To prepare 5-fold dilutions for percutaneous testing in patients suspected to be at greater risk for systemic allergic reaction, start with a 10,000 BAU/milliliter or 100,000 BAU/milliliter stock concentrate. Proceed as shown in Table 2. The 5-fold dilution series uses 1 milliliter of concentrate added to 4 milliliters of sterile 50% glycerin diluent. Subsequent dilutions are made in a similar manner.

To prepare 5-fold dilutions for intradermal testing and immunotherapy, start with a 10,000 BAU/milliliter or 100,000 BAU/milliliter stock concentrate. Proceed as shown in Table 2. The 5-fold dilution series uses 1 milliliter of concentrate added to 4 milliliters of sterile diluent (glycerin-free diluents for intradermal testing, glycerin-free or 10% glycerin-saline diluents for immunotherapy). Subsequent dilutions are made in a similar manner.

Table 2: 5-fold Dilution Series*
Dilution | Extract | Milliliters of Diluent | Dilution Strength (BAU/mL) | Dilution Strength (BAU/mL)
0 | Concentrate |  | 100,000 | 10,000
1 | 1 mL Concentrate | 4 | 20,000 | 2,000
2 | 1 mL Dilution 1 | 4 | 4,000 | 400
3 | 1 mL Dilution 2 | 4 | 800 | 80
4 | 1 mL Dilution 3 | 4 | 160 | 16
5 | 1 mL Dilution 4 | 4 | 32 | 3.2
6 | 1 mL Dilution 5 | 4 | 6.4 | 0.64

2.2 Diagnostic Testing

Diagnostic testing can be performed via percutaneous or intradermal administration of the Standardized Grass Pollen Allergenic Extracts. A positive skin test reaction should be interpreted in relation to the patient’s history and known exposure to the allergen.

If a skin test with a grass pollen extract mixture elicits a positive reaction, then the single-species grass pollen extracts can be used to determine the degree of sensitivity to each individual grass species and to guide in the selection of extracts and their concentration for immunotherapy, if indicated.

Percutaneous Skin Testing

Determine the patient’s sensitivity to the grass pollen allergens.

Preparation and Dose

For percutaneous testing (prick or puncture), use 10,000 or 100,000 BAU/milliliter stock concentrates. If a lower concentration is desired in patients suspected to be at greater risk for a systemic allergic reaction, 10-fold or 5‑fold dilutions of the concentrate can be tested.

Prick test: Place one drop of extract with appropriate controls on the skin and, with a skin test device, pierce through the drop into the skin with a slight lifting motion. Alternatively, use skin test devices loaded with the extract from the storage trays in a similar manner or in accordance with the device manufacturer’s recommendations.

Puncture test: Place one drop of extract or control on the skin and pierce the skin through the drop with a skin test device perpendicular to the skin. Alternatively, use skin test devices loaded with the extract from the storage trays in a similar manner, or in accordance with the device manufacturer’s recommendations.

Interpreting Results

When using percutaneous skin test devices, follow the directions provided with the test devices. A glycerinated histamine control solution (6 milligrams/milliliter or 1 milligram/milliliter histamine base) may be used as the positive control. A 50% glycerin-saline solution may be used as the negative control.

Read and record skin test responses 15 to 20 minutes after exposure. Individual patient reactivity can vary with time, allergen potency, and/or immunotherapy, as well as testing technique. The most reliable method of recording a skin test reaction is to measure the largest diameter of both wheal and erythema. While some correlation exists between the size of the skin test reaction and the degree of sensitivity, other factors should be considered in the diagnosis of allergy to specific allergens (see Figure 1 below).

Figure 1: Measurement of Wheal and Flare

Use a paper or plastic millimeter skin reaction guide as shown below.

Fifteen minutes after application of the skin test, measure the length and midpoint orthogonal width of each flare and wheal from the inner edge of the reaction.

The length of the skin test is defined as the largest diameter and the width of the skin test is defined as the diameter perpendicular to the length at its midpoint. Consider the wheal and flare as separate entities. First, measure the flare and then independently measure the wheal.

Measuring the Flare

Measuring the Wheal

The average diameter measurement in the example above of the flare is (26 mm + 36 mm)/2 = 31 mm and the average diameter of the wheal is (10 mm + 16 mm)/2 = 13 mm.

Responses to positive controls should be at least 3 millimeters larger than responses to the negative controls.

Negative controls should elicit no reaction or only reactions of small diameters (less than 2 millimeters wheal, less than 5 millimeters erythema).

If either the positive or negative control response does not meet the above criteria, results for the allergenic extracts tested at the same time should be considered invalid and be repeated.

Intradermal Skin Testing

Preparation and Dose

For intradermal testing, use 10,000 BAU/milliliter or 100,000 BAU/milliliter of Standardized Grass Pollen Allergenic Extracts stock concentrate solution. Dilute the stock concentrate solution with sterile diluent [see Dosage and Administration (2.1)]. Use normal or buffered saline or normal saline with human serum albumin (HSA) diluent. If the result from the initial test dose is negative, subsequent intradermal tests using increasingly stronger doses may be performed up to the maximum recommended strength of 200 BAU/milliliters dilution of the extract concentrate solution.

Inject 0.02 milliliters of the extract solution intradermally according to the algorithm shown in Figure 2:

Figure 2: Algorithm for Dilution of Stock Concentration Solution of Standardized Grass Pollen Allergenic Extracts for Intradermal Skin Testing

2.3 Immunotherapy

For subcutaneous administration only.

Preparation and Dose

Stock concentrates of GREER Standardized Grass Pollen Allergenic Extracts are available at 10,000 BAU/milliliter or 100,000 BAU/milliliter in 50% glycerin-saline for immunotherapy. Stock concentrates are diluted in normal saline, buffered saline, HSA-saline, or 10% glycerin-saline, depending on the patient’s reactivity to the diluent. See Table 1 and Table 2 for dilution preparation.

Administration of Immunotherapy

Administer immunotherapy by subcutaneous injection in the lateral aspect of the upper arm or thigh. Avoid injection directly into any blood vessel.

The optimal interval between doses of allergenic extract varies among individuals. Injections are usually given 1 to 2 times per week until the maintenance dose is reached, at which time the injection interval is increased to 2, then 3, and finally 4 weeks. Dosages vary by mode of administration, and by clinical response and tolerance. The minimum course of treatment may be three to five years, depending on the clinical response.

Guidelines for Immunotherapy

The initial dose of the extract should be based on the skin test reactivity. In patients suspected to be at greater risk for systemic allergic reaction by history and skin test, the initial dose of the extract should be 0.05 to 0.1 milliliter of a 0.1 to 0.64 BAU/milliliter extract dilution. Patients not suspected to be at greater risk for systemic allergic reaction may be started at a 0.1 milliliter of a 10 to 16 BAU/milliliter extract dilution.

The dose of allergenic extract is increased at each injection by no more than 50% of the previous dose, and the next increment is governed by the response to the last injection.

Select the maximum tolerated maintenance dose based on the patient's clinical response and tolerance. Doses larger than 0.2 milliliter of the stock concentrate are rarely administered because an extract mixed in 50% glycerin diluent can cause discomfort upon injection.

Dosage Modification Guidelines for Immunotherapy

The following conditions may indicate a need to withhold or reduce the dosage of immunotherapy.

- Symptoms of rhinitis and/or asthma
- Infection accompanied by fever
- Exposure to excessive amounts of clinically relevant environmental allergen prior to a scheduled injection
- Large local reactions that persist for longer than 24 hours can be an indication for repeating the previous dose or reducing the dose at the next administration

Any evidence of a systemic adverse reaction is an indication for a significant reduction (at least 75%) in the subsequent dose. Repeated systemic adverse reactions are sufficient reason for the cessation of further attempts to increase the dose.

Local adverse reactions require a decrease in the next dose by at least 50%. Proceed cautiously in subsequent dosing. In situations prompting dose reduction, once the reduced dose is tolerated, a cautious increase in dosage can be attempted.

Changing extract to a different lot or from a different manufacturer: When switching to a different lot of extract, or from another manufacturer’s extract, decrease the starting dose. Because manufacturing processes and sources of raw materials differ among manufacturers, the interchangeability of extracts from different manufacturers cannot be assured. In general, a dose reduction of 50 to 75% of the previous dose should be adequate, but each situation must be evaluated separately, considering the patient’s history of sensitivity, tolerance of previous injections, and other factors. Dose intervals should not exceed one week when rebuilding the dose.

Unscheduled gaps between treatments: Patients can lose tolerance to allergen injections during prolonged periods between doses which increases their risk for an adverse reaction. The duration of tolerance between injections varies from patient to patient.

During the build-up phase, when patients receive injections 1 to 2 times per week, repeat or reduce the extract dosage if there has been a substantial time interval between injections. This depends on: 1) the concentration of allergen immunotherapy extract that is to be administered; 2) a previous history of systemic reactions; and 3) the degree of variation from the prescribed interval of time, with longer intervals since the last injection leading to greater reductions in the dose to be administered.

This suggested approach to dose modification, due to unscheduled gaps between treatments during the build-up phase, is not based on published evidence. The individual physician should use this or a similar protocol for the specific clinical setting.

Similarly, if unscheduled gaps occur during maintenance therapy, it may be necessary to reduce the dosage and bring the patient up to maintenance dosing using an established build-up protocol.

Changing from non-stabilized to human serum albumin (HSA) stabilized diluents: Allergenic extracts prepared with diluents containing HSA and 0.4% phenol are more stable than those prepared with diluents that do not contain stabilizers. When switching from a non-stabilized to an HSA-stabilized diluent, consider lowering the dose for immunotherapy.

3 DOSAGE FORMS AND STRENGTHS

Standardized Bermuda Grass Pollen Allergenic Extract solution is available only at 10,000 Bioequivalent Allergy Units (BAU)/milliliter.

Other Standardized Grass Pollen Allergenic Extract solutions are available as stock concentrates at 10,000 and 100,000 BAU/milliliter.

4 CONTRAINDICATIONS

Standardized Grass Pollen Allergenic Extracts are contraindicated in patients with:

- Severe, unstable or uncontrolled asthma
- History of any severe systemic allergic reaction or any severe local reaction to subcutaneous allergen immunotherapy

5 WARNINGS AND PRECAUTIONS

5.1 Serious Systemic Adverse Reactions

Serious systemic adverse reactions have occurred following the administration of other allergenic extracts and may occur in individuals following the administration of Standardized Grass Pollen Allergenic Extracts in the following situations:

- Extreme sensitivity to grass pollen allergenic extracts
- Receipt of an accelerated immunotherapy build-up schedule (e.g., “rush” immunotherapy)
- Receipt of high doses of grass pollen allergenic extracts or concomitant exposure to similar environmental allergens
- Change from one allergenic lot to another allergenic lot

High-risk patients have had fatal reactions. Consider using more dilute preparations in patients suspected to be at greater risk of systemic allergic reaction [see Dosage and Administration (2.1)].

Administer Standardized Grass Pollen Allergenic Extracts in a healthcare setting under the supervision of a physician prepared to manage a severe systemic or a severe local allergic reaction. Observe patients in the office for at least 30 minutes following administration.^1

5.2 Epinephrine

Standardized Grass Pollen Allergenic Extracts may not be suitable for patients with certain medical conditions that may reduce the ability to survive a serious allergic reaction or increase the risk of adverse reactions after epinephrine administration. Examples of these medical conditions include but are not limited to: markedly compromised lung function (either chronic or acute), unstable angina, recent myocardial infarction, significant arrhythmia, and uncontrolled hypertension.

These products may not be suitable for patients who are taking medications that can potentiate or inhibit the effect of epinephrine. These medications include:

Βeta-adrenergic blockers: Patients taking beta-adrenergic blockers may be unresponsive to the usual doses of epinephrine used to treat serious systemic reactions, including anaphylaxis. Specifically, beta-adrenergic blockers antagonize the cardiostimulating and bronchodilating effects of epinephrine.

Alpha-adrenergic blockers, ergot alkaloids: Patients taking alpha-adrenergic blockers may be unresponsive to the usual doses of epinephrine used to treat serious systemic reactions, including anaphylaxis. Specifically, alpha-adrenergic blockers antagonize the vasoconstricting and hypertensive effects of epinephrine. Similarly, ergot alkaloids may reverse the pressor effects of epinephrine.

Tricyclic antidepressants, levothyroxine sodium, monoamine oxidase inhibitors, and certain antihistamines: The adverse effects of epinephrine may be potentiated in patients taking tricyclic antidepressants, levothyroxine sodium, monoamine oxidase inhibitors, and the antihistamines chlorpheniramine, and diphenhydramine.

Cardiac glycosides, diuretics: Patients who receive epinephrine while taking cardiac glycosides or diuretics should be observed carefully for the development of cardiac arrhythmias.

5.3 Cross-Reactions and Dose Sensitivity

Since many grass species tend to cross-react, the total allergen content should be considered in determining the maximum maintenance dose of the mixture.

Determine the initial dilution of allergenic extract, starting dose, and progression of dosage based on the patient’s history and results of skin tests [see Dosage and Administration (2.2)].^2 Strongly positive skin tests can be indicators for potential systemic reactions.

6 ADVERSE REACTIONS

The most common adverse reactions, occurring in 26 to 82% of all patients who receive subcutaneous immunotherapy are local adverse reactions at the injection site (e.g., erythema, itching, swelling, tenderness, pain).^1 Systemic adverse reactions, occurring in 7% of patients who receive subcutaneous immunotherapy,^3 include generalized skin erythema, urticaria, pruritus, angioedema, rhinitis, wheezing, laryngeal edema, and hypotension. These adverse reactions can be fatal.^1

7 DRUG INTERACTIONS

7.1 Antihistamines

Do not perform skin testing with allergenic extracts within 3 to 10 days of use of first-generation H1-histamine receptor blockers (e.g., clemastine, diphenhydramine) and second-generation antihistamines (e.g., loratadine, cetirizine). These products suppress histamine skin test reactions and could mask a positive response.^2

7.2 Topical Corticosteroids and Topical Anesthetics

Topical corticosteroids can suppress skin reactivity; therefore, discontinue use at the skin test site for 2 to 3 weeks before skin testing. Avoid use of topical local anesthetics at skin test sites as they can suppress flare responses.^2

7.3 Tricyclic Antidepressants

Tricyclic antidepressants can have potent antihistamine effects that can affect skin testing. If tricyclic medication has been recently discontinued, allow 7 to 14 days before initiating skin testing.^2

8 USE IN SPECIFIC POPULATIONS

8.1 Pregnancy

Risk Summary

All pregnancies have a risk of birth defect, loss, or other adverse outcomes. In the U.S. general population, the estimated background risk of major birth defects and miscarriage in clinically recognized pregnancies is 2 to 4% and 15 to 20%, respectively. There are no human or animal data to establish the presence or absence of Standardized Grass Pollen Allergenic Extracts-associated risks during pregnancy.

8.2 Lactation

Risk Summary

It is not known whether Standardized Grass Pollen Allergenic Extracts are present in human milk. Data are not available to assess the effects of these extracts on the breastfed child or on milk production/excretion. The developmental and health benefits of breastfeeding should be considered along with the mother’s clinical need for Standardized Grass Pollen Allergenic Extracts and any potential adverse effects on the breastfed child from the extracts or from the underlying maternal condition.

8.4 Pediatric Use

For use of these products in children younger than 5 years of age, consideration should be given to the patients’ ability to comply and cooperate with allergen immunotherapy and the potential for difficulty in communicating with the child regarding systemic reactions.^1

8.5 Geriatric Use

Data are not available to determine if subjects 65 years of age and older respond differently to allergen immunotherapy than younger subjects.

11 DESCRIPTION

Standardized Grass Pollen Allergenic Extracts include Standardized Bermuda Grass Pollen (Cynodon dactylon) at 10,000 BAU/milliliter, 50% glycerin volume/volume, and 0.4% phenol (preservative); and the following grasses at both 10,000 BAU/milliliter and 100,000 BAU/milliliter, 50% glycerin volume/volume, and 0.4% phenol: Standardized Kentucky Blue (June) Grass Pollen (Poa pratensis), Standardized Meadow Fescue Grass Pollen (Festuca elatior), Standardized Orchard Grass Pollen (Dactylis glomerata), Standardized Perennial Rye Grass Pollen (Lolium perenne), Standardized Redtop Grass Pollen (Agrostis alba), Standardized Sweet Vernal Grass Pollen (Anthoxanthum odoratum), and Standardized Timothy Grass Pollen (Phleum pratense). Inactive ingredients include 0.25% sodium chloride for isotonicity and 0.25% sodium bicarbonate as a buffer.

Standardized Grass Pollen Allergenic Extracts should be clear light yellow to brownish solutions that are free of particulate matter.

Standardized Grass Pollen Allergenic Extracts are labeled in BAU/milliliter. Bioequivalent Allergy Units are assigned based on comparison by enzyme-linked immunosorbent assay (ELISA) to references from the U.S. Food and Drug Administration, Center for Biologics Evaluation and Research (CBER). CBER references are assigned unitage based on quantitative skin testing.^4,5,6,7 CBER references which can be diluted 1:5,000,000 to intradermally elicit a 50 millimeter sum of erythema diameter response in highly puncture reactive subjects are assigned 100,000 BAU/milliliter; whereas references diluted 1:500,000 which elicit the same 50 millimeter sum of erythema diameter response are assigned 10,000 BAU/milliliter.

12 CLINICAL PHARMACOLOGY

12.1 Mechanism of Action

The skin test reaction results from interaction of the introduced allergen and allergen-specific IgE antibodies bound to mast cells, leading to mast cell degranulation and release of histamine, tryptase and other mediators, which results in the formation of the wheal and flare.

The precise mechanisms of action of allergen immunotherapy are not known. Immunologic responses to immunotherapy include changes in allergen-specific IgE levels, allergen-specific IgG levels, and regulatory T cell responses.^1

14 CLINICAL STUDIES

Specific immunotherapy with pollen extracts is helpful in reducing symptoms associated with exposure to the offending allergens. A summary of effectiveness by the Panel on Review of Allergenic Extracts, an advisory committee to the U.S. Food and Drug Administration, has been published.^8

15 REFERENCES

1. Cox L, Nelson H, Lockey R. Allergen immunotherapy: a practice parameter third update. J Allergy Clin Immunol. 2011:S1-S55.
2. Bernstein IL, Li JT, Bernstein DI, et al. Allergy diagnostic testing: an updated practice parameter. Ann Allergy Asthma Immunol. 2008;100:S1-148.
3. Greenberg MA, Kaufman CR, Gonzalez GE, et al. Late and immediate systemic-allergic reactions to inhalant allergen immunotherapy. J Allergy Clin Immunol. 1986;77:865-870.
4. Turkeltaub PC, Rastogi SC, Baer H, et al. A standardized quantitative skin-test assay of allergen potency and stability: studies on the allergen dose-response curve and effect of wheal, erythema, and patient selection on assay results. J Allergy Clin Immunol. 1982; 70:343-352.
5. ELISA competition assay. Methods of the Allergenic Products Testing Laboratory. Rockville, MD: Laboratory of Immunobiochemistry, Division of Allergenic Products and Parasitology, Center for Biologics Evaluation and Research, Food and Drug Administration; October 1993. (On file)
6. Turkeltaub PC, Rastogi SC. Quantitative intradermal procedure for evaluation of subject sensitivity to standardized allergenic extracts and for assignment of bioequivalent allergy units to reference preparations using the ID50EAL method. Rockville, MD: Laboratory of Immunobiochemistry, Division of Allergenic Products and Parasitology, Center for Biologics Evaluation and Research, Food and Drug Administration; November 1994. (On file)
7. Turkeltaub PC. Assignment of bioequivalent allergy units based on biological standardization methods. Arb Paul Ehrlich Inst Bundesamt Sera Impfstoffe Frankf A M. 1988;(82):19-40.
8. Implementation of Efficacy Review, Allergenic Extracts, Federal Register 1985; 50: 3082-3288.

16 HOW SUPPLIED/STORAGE AND HANDLING

16.1 How Supplied

GREER Standardized Grass Pollen Allergenic Extracts and mixes are supplied as stock concentrates at 10,000 BAU/milliliter and 100,000 BAU/milliliter in 50% glycerin for use in percutaneous skin testing, intradermal testing, and subcutaneous immunotherapy. Standardized Grass Pollen Allergenic Extracts are labeled in BAU/milliliter and are provided in 5, 10, and 50 milliliter vials. Note, the total potency of mixes containing standardized grasses may be cumulative.

Standardized Bermuda Grass Pollen Allergenic Extract solution is available only at 10,000 BAU/milliliter.

GREER Standardized Grass Pollen Allergenic Extracts and mixes are supplied as follows:

Standardized Bermuda Grass Pollen (Cynodon dactylon)
NDC Number | Strength/Container
22840-0200-5 | 10,000 BAU/mL, 5 mL dropper vial for prick (skin) testing
22840-0200-2 | 10,000 BAU/mL, 10 mL multiple-dose vials
22840-0200-4 | 10,000 BAU/mL, 50 mL multiple-dose vials
Standardized Bluegrass, Kentucky (June) Grass Pollen (Poa pratensis)
NDC Number | Strength/Container
22840-0201-5 | 10,000 BAU/mL, 5 mL dropper vial for prick (skin) testing
22840-0201-2 | 10,000 BAU/mL, 10 mL multiple-dose vials
22840-0201-4 | 10,000 BAU/mL, 50 mL multiple-dose vials
22840-0202-5 | 100,000 BAU/mL, 5 mL dropper vial for prick (skin) testing
22840-0202-2 | 100,000 BAU/mL, 10 mL multiple-dose vials
22840-0202-4 | 100,000 BAU/mL, 50 mL multiple-dose vials
Standardized Meadow Fescue Grass Pollen (Festcua elatoir)
NDC Number | Strength/Container
22840-0203-5 | 10,000 BAU/mL, 5 mL dropper vial for prick (skin) testing
22840-0203-2 | 10,000 BAU/mL, 10 mL multiple-dose vials
22840-0203-4 | 10,000 BAU/mL, 50 mL multiple-dose vials
22840-0204-5 | 100,000 BAU/mL, 5 mL dropper vial for prick (skin) testing
22840-0204-2 | 100,000 BAU/mL, 10 mL multiple-dose vials
22840-0204-4 | 100,000 BAU/mL, 50 mL multiple-dose vials
Standardized Orchard Grass Pollen (Dactylis glomerata)
NDC Number | Strength/Container
22840-0205-5 | 10,000 BAU/mL, 5 mL dropper vial for prick (skin) testing
22840-0205-2 | 10,000 BAU/mL, 10 mL multiple-dose vials
22840-0205-4 | 10,000 BAU/mL, 50 mL multiple-dose vials
22840-0206-5 | 100,000 BAU/mL, 5 mL dropper vial for prick (skin) testing
22840-0206-2 | 100,000 BAU/mL, 10 mL multiple-dose vials
22840-0206-4 | 100,000 BAU/mL, 50 mL multiple-dose vials
Standardized Perennial Rye Grass Pollen (Lolium perenne)
NDC Number | Strength/Container
22840-0209-5 | 10,000 BAU/mL, 5 mL dropper vial for prick (skin) testing
22840-0209-2 | 10,000 BAU/mL, 10 mL multiple-dose vials
22840-0209-4 | 10,000 BAU/mL, 50 mL multiple-dose vials
22840-0210-5 | 100,000 BAU/mL, 5 mL dropper vial for prick (skin) testing
22840-0210-2 | 100,000 BAU/mL, 10 mL multiple-dose vials
22840-0210-4 | 100,000 BAU/mL, 50 mL multiple-dose vials
Standardized Redtop Grass Pollen (Agrostis alba)
NDC Number | Strength/Container
22840-0207-5 | 10,000 BAU/mL, 5 mL dropper vial for prick (skin) testing
22840-0207-2 | 10,000 BAU/mL, 10 mL multiple-dose vials
22840-0207-4 | 10,000 BAU/mL, 50 mL multiple-dose vials
22840-0208-5 | 100,000 BAU/mL, 5 mL dropper vial for prick (skin) testing
22840-0208-2 | 100,000 BAU/mL, 10 mL multiple-dose vials
22840-0208-4 | 100,000 BAU/mL, 50 mL multiple-dose vials
Standardized Sweet Vernal Grass Pollen (Anthoxanthum odoratum)
NDC Number | Strength/Container
22840-0211-5 | 10,000 BAU/mL, 5 mL dropper vial for prick (skin) testing
22840-0211-2 | 10,000 BAU/mL, 10 mL multiple-dose vials
22840-0211-4 | 10,000 BAU/mL, 50 mL multiple-dose vials
22840-0212-5 | 100,000 BAU/mL, 5 mL dropper vial for prick (skin) testing
22840-0212-2 | 100,000 BAU/mL, 10 mL multiple-dose vials
22840-0212-4 | 100,000 BAU/mL, 50 mL multiple-dose vials
Standardized Timothy Grass Pollen (Phelum pratense)
NDC Number | Strength/Container
22840-0213-5 | 10,000 BAU/mL, 5 mL dropper vial for prick (skin) testing
22840-0213-2 | 10,000 BAU/mL, 10 mL multiple-dose vials
22840-0213-4 | 10,000 BAU/mL, 50 mL multiple-dose vials
22840-0214-5 | 100,000 BAU/mL, 5 mL dropper vial for prick (skin) testing
22840-0214-2 | 100,000 BAU/mL, 10 mL multiple-dose vials
22840-0214-4 | 100,000 BAU/mL, 50 mL multiple-dose vials
Standardized Timothy - Orchard Grass Pollen Mix (equal parts mix)
NDC Number | Strength/Container
22840-0226-2 | 10,000 BAU/mL, 10 mL multiple-dose vials
22840-0215-5 | 100,000 BAU/mL, 5 mL dropper vial for prick (skin) testing
22840-0215-2 | 100,000 BAU/mL, 10 mL multiple-dose vials
22840-0215-4 | 100,000 BAU/mL, 50 mL multiple-dose vials
Standardized K-O-T Grass Pollen Mix (equal parts mix of Kentucky, Orchard, and Timothy pollens)
NDC Number | Strength/Container
22840-0216-5 | 10,000 BAU/mL, 5 mL dropper vial for prick (skin) testing
22840-0216-2 | 10,000 BAU/mL, 10 mL multiple-dose vials
22840-0216-4 | 10,000 BAU/mL, 50 mL multiple-dose vials
22840-0217-5 | 100,000 BAU/mL, 5 mL dropper vial for prick (skin) testing
22840-0217-2 | 100,000 BAU/mL, 10 mL multiple-dose vials
22840-0217-4 | 100,000 BAU/mL, 50 mL multiple-dose vials
Standardized K-O-R-T Grass Pollen Mix (equal parts mix of Kentucky, Orchard, Redtop, and Timothy pollens)
NDC Number | Strength/Container
22840-0218-5 | 10,000 BAU/mL, 5 mL dropper vial for prick (skin) testing
22840-0218-2 | 10,000 BAU/mL, 10 mL multiple-dose vials
22840-0218-4 | 10,000 BAU/mL, 50 mL multiple-dose vials
22840-0219-5 | 100,000 BAU/mL, 5 mL dropper vial for prick (skin) testing
22840-0219-2 | 100,000 BAU/mL, 10 mL multiple-dose vials
22840-0219-4 | 100,000 BAU/mL, 50 mL multiple-dose vials
Standardized K-O-R-T & Sweet Vernal Pollen Mix (equal parts mix of Kentucky, Orchard, Redtop, Timothy and Sweet Vernal pollens)
NDC Number | Strength/Container
22840-0220-5 | 10,000 BAU/mL, 5 mL dropper vial for prick (skin) testing
22840-0220-2 | 10,000 BAU/mL, 10 mL multiple-dose vials
22840-0220-4 | 10,000 BAU/mL, 50 mL multiple-dose vials
22840-0221-5 | 100,000 BAU/mL, 5 mL dropper vial for prick (skin) testing
22840-0221-2 | 100,000 BAU/mL, 10 mL multiple-dose vials
22840-0221-4 | 100,000 BAU/mL, 50 mL multiple-dose vials
Standardized 7 Grass Pollen Mix (equal parts mix of Kentucky, Meadow Fescue, Orchard, Perennial Ryegrass, Redtop, Sweet Vernal and Timothy pollens)
NDC Number | Strength/Container
22840-0222-5 | 10,000 BAU/mL, 5 mL dropper vial for prick (skin) testing
22840-0222-2 | 10,000 BAU/mL, 10 mL multiple-dose vials
22840-0222-4 | 10,000 BAU/mL, 50 mL multiple-dose vials
22840-0223-5 | 100,000 BAU/mL, 5 mL dropper vial for prick (skin) testing
22840-0223-2 | 100,000 BAU/mL, 10 mL multiple-dose vials
22840-0223-4 | 100,000 BAU/mL, 50 mL multiple-dose vials
Standardized T-O-S Grass Pollen Mix (equal parts mix of Timothy, Orchard and Sweet Vernal pollens)
NDC Number | Strength/Container
22840-0224-5 | 10,000 BAU/mL, 5 mL dropper vial for prick (skin) testing
22840-0227-5 | 100,000 BAU/mL, 5 mL dropper vial for prick (skin) testing
22840-0227-2 | 100,000 BAU/mL, 10 mL multiple-dose vials
22840-0227-4 | 100,000 BAU/mL, 50 mL multiple-dose vials
9 Southern Grass Pollen Mix [equal parts mix of 10,000 BAU/mL Bermuda and 100,000 BAU/mL each Kentucky, Meadow Fescue, Orchard, Perennial Rye, Redtop, Sweet Vernal, Timothy pollens and non-standardized Johnson Grass (Sorghum halpense) pollen extract]
NDC Number | Strength/Container
22840-0225-5 | Concentrate, 5 mL dropper vial for prick (skin) testing
22840-0225-2 | Concentrate, 10 mL multiple-dose vials
22840-0225-4 | Concentrate, 50 mL multiple-dose vials

16.2 Storage and Handling

Maintain at 2 to 8°C (36 to 46°F) during storage and use.

Dilutions of concentrated extract result in a glycerin content of less than 50%, which can result in reduced stability. Extract dilutions at 1:100 volume/volume of the 10,000 BAU/milliliter or 100,000 BAU/milliliter should be kept no longer than a month, and more dilute solutions no more than a week. The potency of a dilution can be checked by skin test comparison to a fresh dilution of the extract on a known grass-allergic patient.

17 PATIENT COUNSELING INFORMATION

Instruct patient to remain under observation in the office for 30 minutes or longer after an injection.

Caution patient that reactions can occur more than 30 minutes after skin testing or an injection.

Instruct patient to recognize the following symptoms as adverse reactions and to immediately return to the office or immediately seek other medical attention if any of these symptoms occur following skin testing or an injection:

- Unusual swelling and/or tenderness at the injection site
- Hives or itching of the skin
- Swelling of face and/or mouth
- Sneezing, coughing or wheezing
- Shortness of breath
- Nausea
- Dizziness or faintness

Manufacturer:

U.S. License No. 308
Greer Laboratories, Inc.
Lenoir, NC 28645 U.S.A